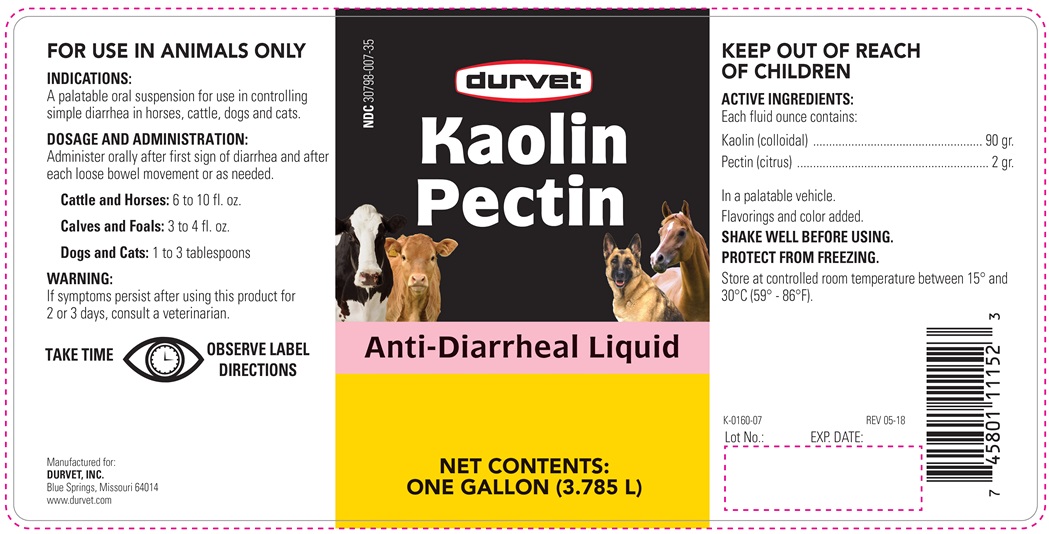 DRUG LABEL: KAOLIN-PECTIN
NDC: 30798-007 | Form: SUSPENSION
Manufacturer: Durvet, Inc.
Category: animal | Type: OTC ANIMAL DRUG LABEL
Date: 20180702

ACTIVE INGREDIENTS: KAOLIN 5.8 g/29.57 mL; PECTIN 0.13 g/29.57 mL

KAOLIN-PECTIN

INDICATIONS AND USAGE

ANTI-DIARRHEAL LIQUID

FOR ANIMAL USE ONLY

KEEP OUT OF REACH OF CHILDREN

INDICATIONS

A palatable oral suspension for use in controlling simple diarrhea in horses, cattle, dogs and cats.

DOSAGE AND ADMINISTRATION

Administer orally after first sign of diarrhea and after each loose bowel movement or as needed.

Cattle and Horses: 6 to 10 fl. ozs.

Calves and Foals: 3 to 4 fl. ozs.

Dogs and Cats: 1 to 3 tablespoons

WARNING

If symptoms persist after using this product for 2 or 3 days, consult a veterinarian.

ACTIVE INGREDIENTS

EACH FLUID OUNCE CONTAINS

Kaolin (colloidal) ................................ 90 gr.

Pectin (citrus) ..................................... 2 gr.

In a palatable vehicle. Flavorings and color added.

STORAGE AND HANDLING

SHAKE WELL BEFORE USING

PROTECT FROM FREEZING.

TAKE TIME OBSERVE LABEL DIRECTIONS.

Store in a controlled room temperature between 15° and 30°C (59° - 86°F)